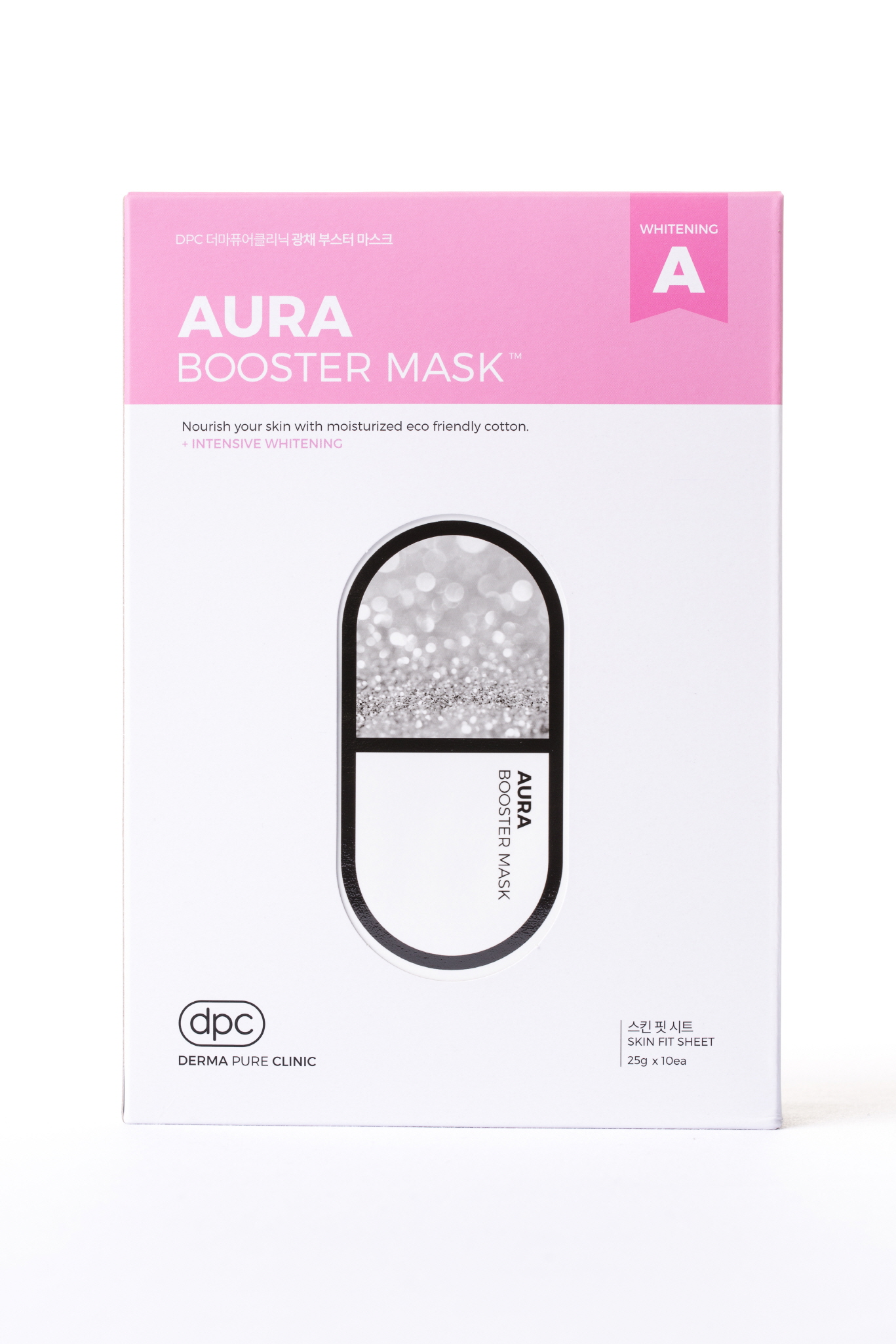 DRUG LABEL: DPC Aura Booster Mask
NDC: 71673-0001 | Form: LIQUID
Manufacturer: MSCO
Category: otc | Type: HUMAN OTC DRUG LABEL
Date: 20170817

ACTIVE INGREDIENTS: NIACINAMIDE 2 g/100 g
INACTIVE INGREDIENTS: ALLANTOIN; WATER; HYALURONATE SODIUM; GLYCERIN

Drug Facts

ACTIVE INGREDIENT

NIACINAMIDE

INACTIVE INGREDIENT

Water
Glycerin
Butylene Glycol
Sodium Hyaluronate
1,2-Hexanediol
Allantoin
Dipotassium Glycyrrhizate
Trehalose
Hydroxyethylcellulose
Carbomer
PEG-60 Hydrogenated Castor Oil
Glyceryl Acrylate/Acrylic Acid Copolymer
Propylene Glycol
PVM/MA Copolymer
Panthenol
Diamond powder
Simmondsia Chinensis (Jojoba) Seed Oil
Anthemis Nobilis Flower Extract
Jasminum Officinale (Jasmine) Flower Water
Lilium Tigrinum Extract
Arnica Montana Flower Extract
Arginine
Chlorphenesin
Disodium EDTA
Glycyrrhiza Glabra (Licorice) Root Extract
Zingiber Officinale (Ginger) Root Extract
Schizandra Chinensis Fruit Extract
Coptis Japonica Root Extract
Camellia Sinensis Leaf Extract
Caprylyl Glycol
Citrus Grandis (Grapefruit) Seed Extract
Acorus Calamus Root Extract
Perilla Ocymoides Leaf Extract
Fragrance

PURPOSE

Skin Protectant - Intensive Whitening

keep out of reach of the children

INDICATIONS AND USAGE

1. After cleansing wipe water and apply skin lotion on face.
2. Apply the mask evenly over the face for 10-20 minutes and remove.
3. Pad the left over residue lightly to absorb.

WARNINGS

For external use only.
Avoid contact with eyes. Not for human consumption.
Discontinue use if irritation occurs.
If irritation persists, consult a physician.

DOSAGE AND ADMINISTRATION

for external use only